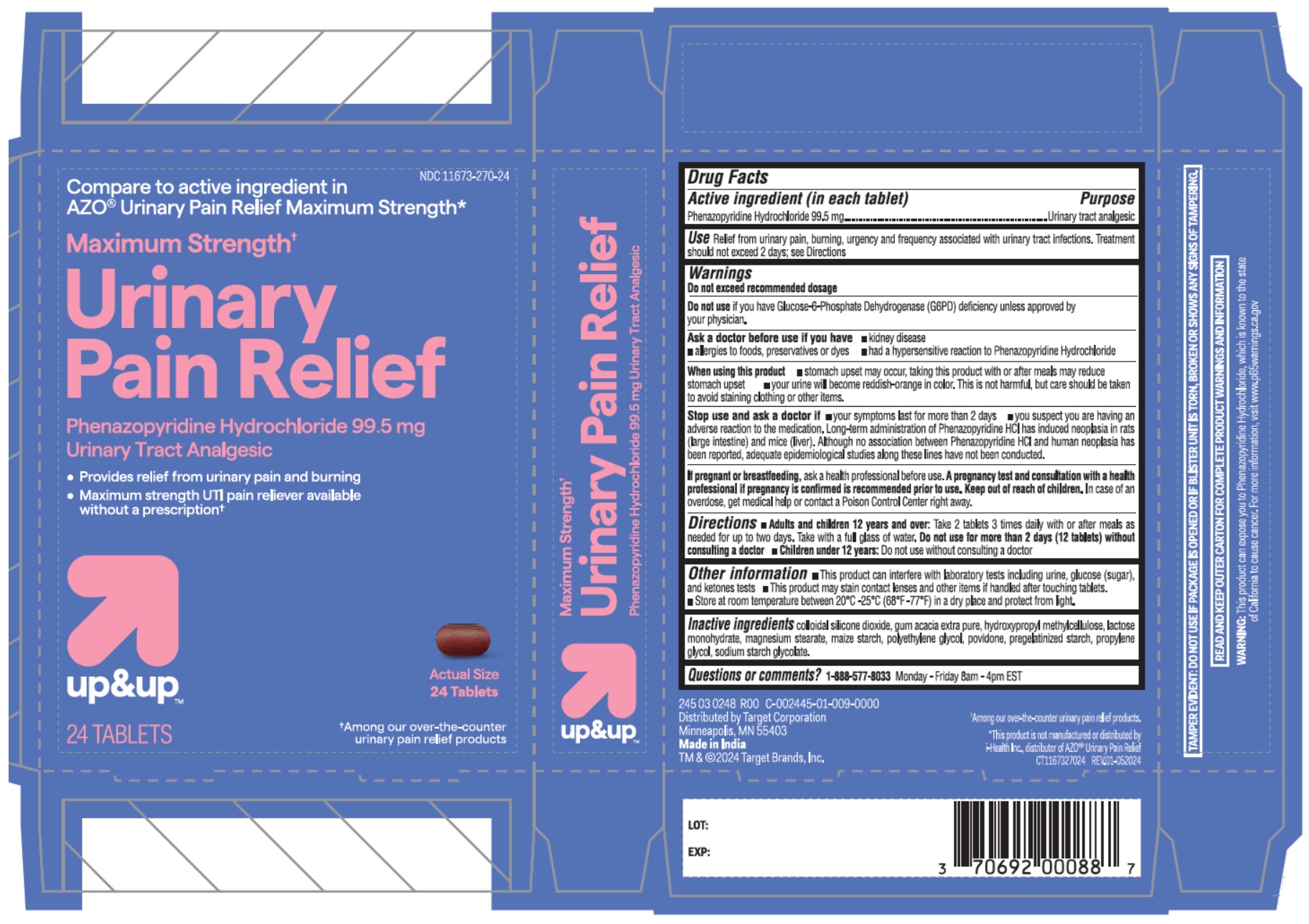 DRUG LABEL: Maximum Strength Urinary Pain Relief
NDC: 11673-270 | Form: TABLET
Manufacturer: TARGET CORPORATION
Category: otc | Type: HUMAN OTC DRUG LABEL
Date: 20251230

ACTIVE INGREDIENTS: PHENAZOPYRIDINE HYDROCHLORIDE 99.5 mg/1 1
INACTIVE INGREDIENTS: SILICON DIOXIDE; ACACIA; HYPROMELLOSE, UNSPECIFIED; LACTOSE MONOHYDRATE; MAGNESIUM STEARATE; STARCH, CORN; POLYETHYLENE GLYCOL, UNSPECIFIED; POVIDONE, UNSPECIFIED; PROPYLENE GLYCOL; SODIUM STARCH GLYCOLATE TYPE A

up&up™ Maximum Strength† Urinary Pain Relief

Active ingredient (in each tablet)

Phenazopyridine Hydrochloride 99.5 mg

Purpose

Urinary tract analgesic

Use

Relief from urinary pain, burning, urgency and frequency associated with urinary tract infections. Treatment should not exceed 2 days; see Directions

Warnings

Do not exceed recommended dosage

Do not use if you have Glucose-6-Phosphate Dehydrogenase (G6PD) deficiency unless approved by your physician.

Ask a doctor before use if you have • kidney disease
• allergies to foods, preservatives or dyes • had a hypersensitive reaction to Phenazopyridine Hydrochloride

When using this product • stomach upset may occur, taking this product with or after meals may reduce stomach upset • your urine will become reddish-orange in color. This is not harmful, but care should be taken to avoid staining clothing or other items.

Stop use and ask a doctor if • your symptoms last for more than 2 days • you suspect you are having an adverse reaction to the medication. Long-term administration of Phenazopyridine HCl has induced neoplasia in rats (large intestine) and mice (liver). Although no association between Phenazopyridine HCl and human neoplasia has been reported, adequate epidemiological studies along these lines have not been conducted.

If pregnant or breastfeeding, ask a health professional before use. A pregnancy test and consultation with a health professional if pregnancy is confirmed is recommended prior to use.

Keep out of reach of children. In case of an overdose, get medical help or contact a Poison Control Center right away.

Directions

• Adults and children 12 years and over: Take 2 tablets 3 times daily with or after meals as needed for up to two days. Take with a full glass of water. Do not use for more than 2 days (12 tablets) without consulting a doctor • Children under 12 years: Do not use without consulting a doctor

Other information

• This product can interfere with laboratory tests including urine, glucose (sugar), and ketones tests • This product may stain contact lenses and other items if handled after touching tablets. • Store at room temperature between 20ºC -25ºC (68ºF-77ºF) in a dry place and protect from light.

Inactive ingredients

colloidal silicon dioxide, gum acacia extra pure, hydroxypropyl methylcellulose, lactose monohydrate, magnesium stearate, maize starch, polyethylene glycol, povidone, pregelatinized starch, propylene glycol, sodium starch glycolate.

Questions or comments?

1-888-577-8033 Monday-Friday 8am-4pm EST

Compare to active ingredient in AZO® Urinary Pain Relief Maximum Strength*

• Provides relief from urinary pain and burning
• Maximum strength UTI pain reliever available without a prescription†

†Among our over-the-counter urinary pain relief products

245 03 0248 ROO C-002445-01-009-0000
Distributed by Target Corporation
Minneapolis, MN 55403
Made in India
TM & ©2024 Target Brands, Inc.

*This product is not manufactured or distributed by i-Health Inc., distributor of AZO® Urinary Pain Relief

TAMPER EVIDENT: DO NOT USE IF PACKAGE IS OPENED OR IF BLISTER UNIT IS TORN, BROKEN OR SHOWS ANY SIGNS OF TAMPERING.

READ AND KEEP OUTER CARTON FOR COMPLETE PRODUCT WARNINGS AND INFORMATION

WARNING: This product can expose you to Phenazopyridine Hydrochloride, which is known to the state of California to cause cancer. For more information, visit www.p65warnings.ca.gov